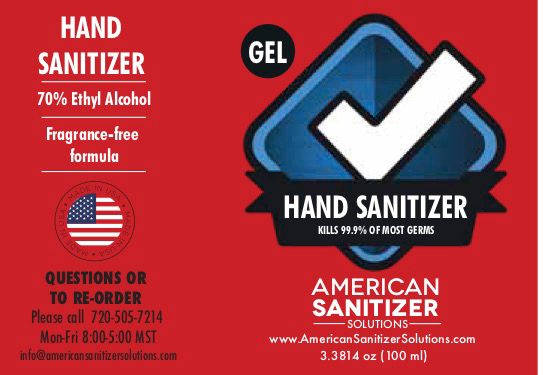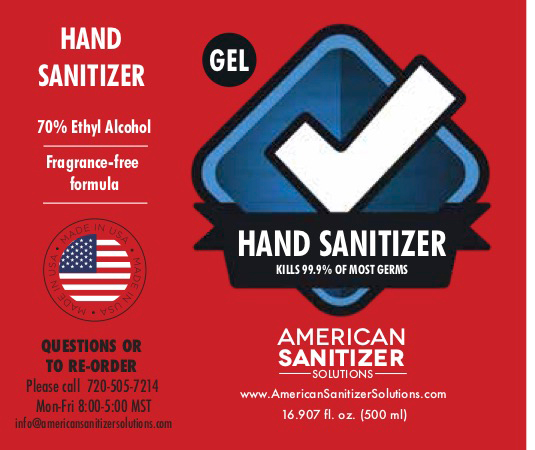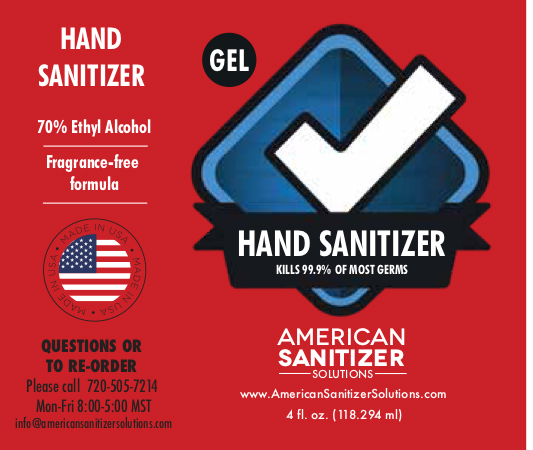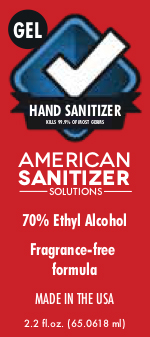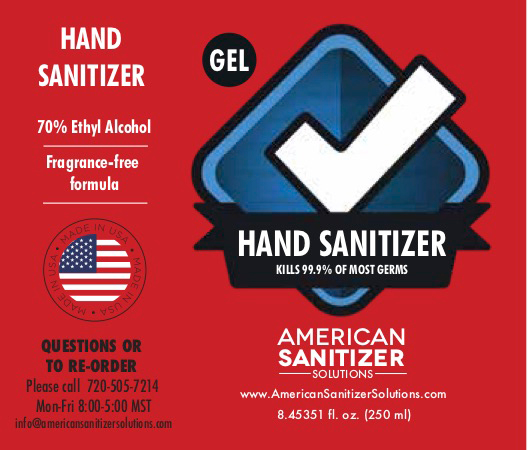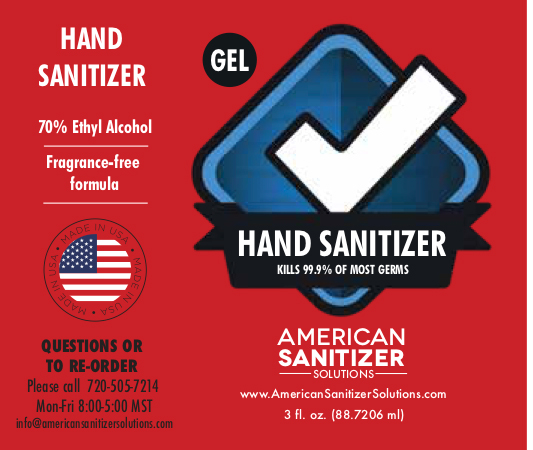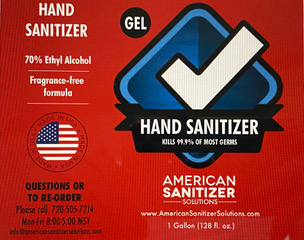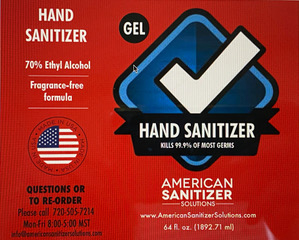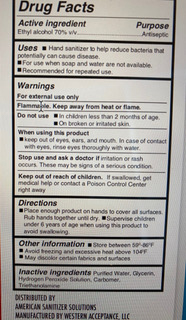 DRUG LABEL: Hand Sanitizer
NDC: 80206-020 | Form: GEL
Manufacturer: Western Acceptance, LLC
Category: otc | Type: HUMAN OTC DRUG LABEL
Date: 20200501

ACTIVE INGREDIENTS: ISOPROPYL ALCOHOL 70 mL/100 mL
INACTIVE INGREDIENTS: TRIETHANOLAMINE LAURYL SULFATE 1 mL/100 mL; GLYCERIN 1.45 mL/100 mL; HYDROGEN PEROXIDE 1 mL/100 mL; WATER 26 mL/100 mL; CARBOMER 940 1 mL/100 mL

Gel Hand Sanitizer

Active Ingredient(s)

Isopropyl Alcohol 70% v/v. Purpose: Antiseptic

Purpose

Antiseptic, Gel Hand Sanitizer

Use

Hand Sanitizer to help reduce bacteria that potentially can cause disease. For use when soap and water are not available.

Warnings

For external use only. Flammable. Keep away from heat or flame

Do not use

- in children less than 2 months of age
- on open skin wounds

When using this product keep out of eyes, ears, and mouth. In case of contact with eyes, rinse eyes thoroughly with water.
Stop use and ask a doctor if irritation or rash occurs. These may be signs of a serious condition.
Keep out of reach of children. If swallowed, get medical help or contact a Poison Control Center right away.

Stop use and ask a doctor if irritation or rash occurs. These may be signs of a serious condition.

Keep out of reach of children. If swallowed, get medical help or contact a Poison Control Center right away.

Directions

- Place enough product on hands to cover all surfaces. Rub hands together until dry.
- Supervise children under 6 years of age when using this product to avoid swallowing.

Other information

- Store between 15-30C (59-86F)
- Avoid freezing and excessive heat above 40C (104F)

Inactive ingredients

purified water USP,glycerin, hydrogen peroxide, carbomer, triethanolamine

Package Label - Principal Display Panel

3785.41 ml NDC: 80206-020-02

1879.71 ml NDC: 80206-020-01

500 ml NDC: 80206-020-03

250ml NDC: 80206-020-04

118.294 ml NDC: 80206-020-05

88.2706 ml NDC: 80206-020-06

100 ml NDC: 80206-020-07

65.0618 ml NDC: 80206-020-08